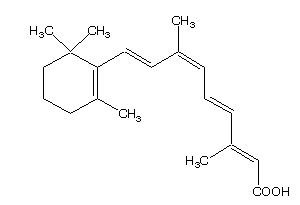 DRUG LABEL: Unknown
Manufacturer: Ligand Pharmaceuticals Incorporated
Category: prescription | Type: HUMAN PRESCRIPTION DRUG LABELING
Date: 20061006

Panretin®
(alitretinoin)
gel 0.1%
(For topical use only)

Description

Panretin® gel 0.1% contains alitretinoin and is intended for topical application only. The chemical name is 9-cis-retinoic acid and the structural formula is as follows:

Chemically, alitretinoin is related to vitamin A. It is a yellow powder with a molecular weight of 300.44 and a molecular formula of C20H28O2. It is slightly soluble in ethanol (7.01 mg/g at 25oC) and insoluble in water. Panretin® gel is a clear, yellow gel containing 0.1% (w/w) alitretinoin in a base of dehydrated alcohol USP, polyethylene glycol 400 NF, hydroxypropyl cellulose NF, and butylated hydroxytoluene NF.

CLINICAL PHARMACOLOGY

Mechanism of Action

Alitretinoin (9-cis-retinoic acid) is a naturally-occurring endogenous retinoid that binds to and activates all known intracellular retinoid receptor subtypes (RARα, RARβ, RARγ, RXRα, RXRβ and RXRγ). Once activated these receptors function as transcription factors that regulate the expression of genes that control the process of cellular differentiation and proliferation in both normal and neoplastic cells. Alitretinoin inhibits the growth of Kaposi’s sarcoma (KS) cells in vitro.

Pharmacokinetics

No studies have examined plasma 9-cis-retinoic acid concentrations before and after treatment with Panretin® gel. There is, however, indirect evidence that absorption is not extensive. Plasma concentrations of 9-cis-retinoic acid were evaluated during clinical studies in patients with cutaneous lesions of AIDS-related KS after repeated multiple-daily dose application of Panretin® gel for up to 60 weeks. The range of 9-cis-retinoic acid plasma concentrations in these patients was similar to the range of circulating, naturally-occurring 9-cis-retinoic acid plasma concentrations in untreated healthy volunteers.

Although there are no detectable plasma concentrations of 9-cis-retinoic acid metabolites after topical application of Panretin® gel, in vitro studies indicate that the drug is metabolized to 4-hydroxy-9-cis-retinoic acid and 4-oxo-9-cis-retinoic acid by CYP 2C9, 3A4, 1A1, and 1A2 enzymes. In vivo, 4-oxo-9-cis-retinoic acid is the major circulating metabolite following oral administration of 9-cis-retinoic acid.

No formal pharmacokinetic drug interaction studies between Panretin® gel and antiretroviral agents have been conducted.

Clinical Studies

Panretin® gel is not a systemic therapy; it therefore cannot treat visceral Kaposi’s sarcoma (KS) nor prevent the development of new KS lesions where it has not been applied. Visceral KS disease was not monitored in these trials, and the appearance of new KS lesions was not considered part of the response assessment in clinical trials.

Panretin® gel was evaluated in two multicenter, prospective, randomized, double-blind, vehicle-controlled studies in patients with cutaneous lesions of AIDS-related KS. In both studies the primary efficacy endpoint was the patients’ cutaneous KS tumor response rate through 12 weeks of study drug treatment which was assessed by evaluating from 3 to 8 KS index lesions according to the modified AIDS Clinical Trials Group (ACTG) response criteria as applied to topical therapy (i.e., evaluation of height and area reductions of the index lesions only; progressive disease in non-index lesions and new lesions were not considered progressive disease; progressive disease was scored only in the treated index lesions). A global evaluation by physicians was also carried out. It considered all of the patient’s treated lesions (index and other) compared to baseline. In this evaluation, patients with at least a 50% improvement in the KS lesions were considered responders. In addition, photographs of lesions in patients considered responders by the modified ACTG criteria were examined by the FDA for a cosmetically beneficial response, defined as at least a 50% improvement in appearance compared to baseline, considering both the KS lesions and dermal toxicity at the lesion site, in at least 50% of the index lesions and maintained for at least 3 weeks. Patients were also asked about their satisfaction with the treatment.

In Study 1, a total of 268 patients were entered from centers in the U.S. and Canada. Patients were treated topically three to four times a day with either Panretin® gel or a matching vehicle gel for a minimum of 12 weeks, followed by an open-label phase in patients who had not yet progressed on Panretin® gel. Responses during the double-blind phase are shown in Table 1. Responses to Panretin® gel were seen in both previously untreated patients and in patients with prior systemic and/or topical KS treatment. A total of 72 patients responded to Panretin® gel during the randomized or crossover portions of the study. At a median duration of monitoring of 16 weeks, only 15% of the 72 patients had relapsed. Panretin® gel would not be expected to affect development of new lesions in untreated areas and these were seen in about 50% of patients, at similar rates in treated and untreated patients, responders and non-responders. The patients’ assessment of their overall satisfaction with the drug effect on all treated lesions significantly favored Panretin® gel.

Study 2 was an international study with a planned enrollment of 270 patients. Patients were treated topically twice a day with Panretin® gel or a matching vehicle for 12 weeks. The study was stopped early because of positive interim results in the initial 82 patient data set. Results of the study are shown in Table 1. Responses to Panretin® gel were seen both in previously untreated patients and in patients with prior systemic and/or topical KS treatment.

TABLE 1: Summary of Tumor Responses
 | STUDY 1 |  | STUDY 2
 | Panretin® Gel; N=134 | Vehicle Gel; N=134 | Panretin® Gel; N=36 | Vehicle Gel; N=46
Modified ACTG Response; (index lesions) | 34% PR; 1% CR | 16% PR; p=0.0012 | 36% PR | 7% PR
Physician's Global/Subjective Assessment; (all treated lesions) | 19% PR | 4% PR; p=0.00014 | 47% PR | 11% PR
Beneficial Response Photographs; (index lesions only) | 15% | 4%; p=0.0026 | 19% | 2%

In the clinical trials, responses were seen as early as two (2) weeks; most patients, however, required four (4) to eight (8) weeks of treatment, and some patients did not experience significant improvement until 14 or more weeks of treatment. The cumulative percentage of patients who achieved a response was less than 1% at 2 weeks, 10% at 4 weeks, and 28% at 8 weeks.

In both studies, responses occurred in patients with a wide range of baseline CD4+ lymphocyte counts, including patients with CD4+ lymphocyte counts less than 50 cells/mm^3. Nearly all patients received concomitant combination antiretroviral therapy.

Photographs of patients revealed a substantial erythematous and edematous response in some cases, leading to a cosmetically mixed outcome even in apparent responders. Nonetheless, in Study 1 it appeared that a cosmetically satisfactory result occurred at about the same rate as the Physician’s Global response rate and in both studies such a response was more frequent than in the vehicle control.

INDICATIONS AND USAGE

Panretin® gel is indicated for topical treatment of cutaneous lesions in patients with AIDS-related Kaposi’s sarcoma. Panretin® gel is not indicated when systemic anti-KS therapy is required (e.g., more than 10 new KS lesions in the prior month, symptomatic lymphedema, symptomatic pulmonary KS, or symptomatic visceral involvement). There is no experience to date using Panretin® gel with systemic anti-KS treatment.

CONTRAINDICATIONS

Panretin® gel is contraindicated in patients with a known hypersensitivity to retinoids or to any of the ingredients of the product.

WARNINGS

PREGNANCY

Pregnancy: Panretin® gel could cause fetal harm if significant absorption were to occur in a pregnant woman. 9-cis-Retinoic acid has been shown to be teratogenic in rabbits and mice. An increased incidence of fused sternebrae and limb and craniofacial defects occurred in rabbits given oral doses of 0.5 mg/kg/day (about five times the estimated daily human topical dose on a mg/m^2 basis, assuming complete systemic absorption of 9-cis-retinoic acid, when Panretin® gel is administered as a 60 g tube over 1 month in a 60 kg human) during the period of organogenesis. Limb and craniofacial defects also occurred in mice given a single oral dose of 50 mg/kg on day eleven of gestation (about 127 times the estimated daily human topical dose on a mg/m^2 basis). Oral 9-cis-retinoic acid was also embryocidal, as indicated by early resorptions and post-implantation loss when it was given during the period of organogenesis to rabbits at doses of 1.5 mg/kg/day (about 15 times the estimated daily human topical dose on a mg/m^2 basis) and to rats at doses of 5 mg/kg/day (about 25 times the estimated daily human topical dose on a mg/m^2 basis). Animal reproduction studies with topical 9-cis-retinoic acid have not been conducted. It is not known whether topical Panretin® gel can modulate endogenous 9-cis-retinoic acid levels in a pregnant woman nor whether systemic exposure is increased by application to ulcerated lesions or by duration of treatment. There are no adequate and well-controlled studies in pregnant women. If Panretin® gel is used during pregnancy, or if the patient becomes pregnant while taking it, the patient should be apprised of the potential hazard to the fetus. Women of child-bearing potential should be advised to avoid becoming pregnant.

PRECAUTIONS

Panretin® gel is indicated for topical treatment of Kaposi’s sarcoma. Patients with cutaneous T-cell lymphoma were less tolerant of topical Panretin® gel; five of seven patients had 6 episodes of treatment-limiting toxicities—grade 3 dermal irritation—with Panretin® gel (0.01% or 0.05%).

Photosensitivity

Retinoids as a class have been associated with photosensitivity. There were no reports of photosensitivity associated with the use of Panretin® gel in the clinical studies. Nonetheless, because in vitro data indicate that 9-cis-retinoic acid may have a weak photosensitizing effect, patients should be advised to minimize exposure of treated areas to sunlight and sunlamps during the use of Panretin® gel.

Drug Interactions

Patients who are applying Panretin® gel should not concurrently use products that contain DEET (N,N-diethyl-m-toluamide), a common component of insect repellent products. Animal toxicology studies showed increased DEET toxicity when DEET was included as part of the formulation.

Although there was no clinical evidence in the vehicle-controlled studies of drug interactions with systemic antiretroviral agents, including protease inhibitors, macrolide antibiotics, and azole antifungals, the effect of Panretin® gel on the steady-state concentrations of these drugs is not known. No drug interaction data are available on concomitant administration of Panretin® gel and systemic anti-KS agents.

Drug/Laboratory Test Interactions

No interference with laboratory tests has been observed.

Carcinogenesis, Mutagenesis, Impairment of Fertility

Long-term studies in animals to assess the carcinogenic potential of 9-cis-retinoic acid have not been conducted. 9-cis-Retinoic acid was not mutagenic in vitro (bacterial assays, Chinese hamster ovary cell HGPRT mutation assay) and was not clastogenic in vitro (chromosome aberration test in human lymphocytes) nor in vivo (mouse micronucleus test).

Nursing Mothers

It is not known whether alitretinoin or its metabolites are excreted in human milk. Because many drugs are excreted in human milk and because of the potential for adverse reactions from Panretin® gel in nursing infants, mothers should discontinue nursing prior to using the drug.

Pediatric Use

Safety and effectiveness in pediatric patients have not been established.

Geriatric Use

Inadequate information is available to assess safety and efficacy in patients age 65 years or older.

ADVERSE REACTIONS

The safety of Panretin® gel has been assessed in clinical studies of 385 patients with AIDS-related KS. Adverse events associated with the use of Panretin® gel in patients with AIDS-related KS occurred almost exclusively at the site of application. The dermal toxicity begins as erythema; with continued application of Panretin® gel, erythema may increase and edema may develop. Dermal toxicity may become treatment-limiting, with intense erythema, edema, and vesiculation. Usually, however, adverse events are mild to moderate in severity; they led to withdrawal from the study in only 7% of the patients. Severe local (application site) skin adverse events occurred in about 10% of patients in the U.S. study (versus 0% in the vehicle control). Table 2 lists the adverse events that occurred at the application site with an incidence of at least 5% during the double-blind phase in the Panretin® gel-treated group and in the vehicle control group in either of the two controlled studies. Adverse events were reported at other sites but generally were similar in the two groups.

TABLE 2: Adverse Events with an Incidence of at Least 5% at the Application Site in Either Controlled Study in Patients Receiving Panretin® Gel or Vehicle Control
Adverse Event Term | Study 1 |  | Study 2
 | Panretin® Gel; N=134 Pts.; % | Vehicle Gel; N=134 Pts.; % | Panretin® Gel; N=36 Pts.; % | Vehicle Gel; N=46 Pts.; %
Rash^1 | 77 | 11 | 25 | 4
Pain^2 | 34 | 7 | 0 | 4
Pruritus^3 | 11 | 4 | 8 | 4
Exfoliative dermatitis^4 | 9 | 2 | 3 | 0
Skin disorder^5 | 8 | 1 | 0 | 0
Paresthesia^6 | 3 | 0 | 22 | 7
Edema^7 | 8 | 3 | 3 | 0
Includes Investigator terms:
^1Erythema, scaling, irritation, redness, rash, dermatitis
^2Burning, pain
^3Itching, pruritus
^4Flaking, peeling, desquamation, exfoliation
^5Excoriation, cracking, scab, crusting, drainage, eschar, fissure or oozing
^6Stinging, tingling
^7Edema, swelling, inflammation

OVERDOSAGE

There has been no experience with acute overdose of Panretin® gel in humans. Systemic toxicity following acute overdosage with topical application of Panretin® gel is unlikely because of limited systemic plasma levels observed with normal therapeutic doses. There is no specific antidote for overdosage.

DOSAGE AND ADMINISTRATION

Panretin® gel should initially be applied two (2) times a day to cutaneous KS lesions. The application frequency can be gradually increased to three (3) or four (4) times a day according to individual lesion tolerance. If application site toxicity occurs, the application frequency can be reduced. Should severe irritation occur, application of drug can be temporarily discontinued for a few days until the symptoms subside.

Sufficient gel should be applied to cover the lesion with a generous coating. The gel should be allowed to dry for three to five minutes before covering with clothing. Because unaffected skin may become irritated, application of the gel to normal skin surrounding the lesions should be avoided. In addition, do not apply the gel on or near mucosal surfaces of the body.

A response of KS lesions may be seen as soon as two weeks after initiation of therapy but most patients require longer application. With continued application, further benefit may be attained. Some patients have required over 14 weeks to respond. In clinical trials, Panretin® gel was applied for up to 96 weeks. Panretin® gel should be continued as long as the patient is deriving benefit.

Occlusive dressings should not be used with Panretin® gel.

How Supplied

Panretin® gel is available in tubes containing 60 grams. Store at 25° C (77° F); excursions permitted to 15-30° C (59-86° F) [see USP Controlled Room Temperature].

Manufactured for: Ligand Pharmaceuticals Incorporated
San Diego, CA 92121

by: Bristol-Myers Squibb Company
Princeton, NJ 08543 USA

NDC 64365-501-01

Ligand Part #3000153 (Rev. 1001)